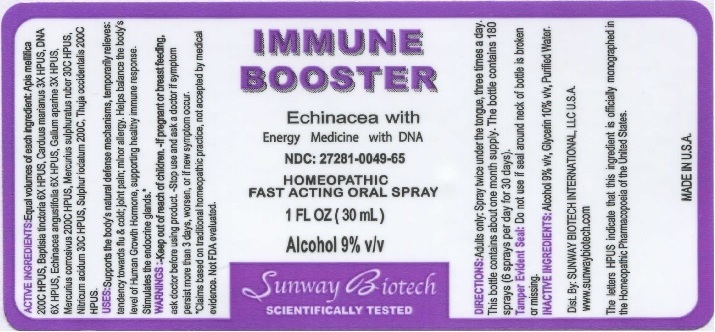 DRUG LABEL: Immune Booster
NDC: 27281-049 | Form: LIQUID
Manufacturer: Sunway Biotech LLC
Category: homeopathic | Type: HUMAN OTC DRUG LABEL
Date: 20211229

ACTIVE INGREDIENTS: APIS MELLIFERA 200 [hp_C]/30 mL; BAPTISIA TINCTORIA ROOT 6 [hp_X]/30 mL; MILK THISTLE 3 [hp_X]/30 mL; ECHINACEA ANGUSTIFOLIA 6 [hp_X]/30 mL; GALIUM APARINE 3 [hp_X]/30 mL; MERCURIC CHLORIDE 200 [hp_C]/30 mL; MERCURIC SULFIDE 30 [hp_C]/30 mL; NITRIC ACID 30 [hp_C]/30 mL; SULFUR IODIDE 200 [hp_C]/30 mL; THUJA OCCIDENTALIS LEAFY TWIG 200 [hp_C]/30 mL
INACTIVE INGREDIENTS: ALCOHOL; GLYCERIN; WATER

Immune Booster

ACTIVE INGREDIENT

ACTIVE INGREDIENTS: Equal volumes of each ingredient: Apis mellifica 200C HPUS, Baptisia tinctoria 6X HPUS, Carduus marianus 3X HPUS, Echinacea angustifolia 6X HPUS, Gallum aparine 3X HPUS, Mercurius corrosivus 200C HPUS, Mercurius sulphuratus ruber 30C HPUS, Nitricum acidum 30C HPUS, Sulphur iodatum 200C, Thuja occidentalis 200C HPUS.

The letters HPUS indicate that ingredient is officially monographed in the Homeopathic Pharmarcopoeia of the United States.

INDICATIONS AND USAGE

USES: Supports the body's natural defense mechanisms, temporarily relieves: tendency towards flu & cold; joint pain; minor allergy. Helps balance the body's level of Human Growth Hormone, supporting healthy immune response. Stimulates the endocrine glands*

*Claims based on traditional homeopathic practice, not accepted by medical evidence. Not FDA evaluated.

WARNINGS

Warnings: If pregnant or breast feeding, ask a doctor before using product. Stop use and ask a doctor if symptom persist more than 3 days, worsen, or if new symptom occur.

- KEEP OUT OF REACH OF CHILDREN.

DOSAGE AND ADMINISTRATION

DIRECTIONS: Adults only: Spray twice under the tongue, three times a day. This bottle contains about a 1 month supply. The bottle contains 180 sprays (6sprays per day for 30 days).

OTHER SAFETY INFORMATION

Tamper Evident Seal: Do not use if seal around neck of bottle is broken or missing.

INACTIVE INGREDIENT

Inactive Ingredients: Alcohol 9% v/v, Glycerin 10% v/v, Purified Water.

QUESTIONS

Dist. By: SUNWAY BIOTECH INTERNATIONAL, LLC U.S.A.

www.sunwaybiotech.com

PACKAGE LABEL

IMMUNE BOOSTER

Echinacea with Energy Medicine with DNA

NDC: 27281-049-65

HOMEOPATHIC FAST ACTING ORAL SPRAY

1 FL OZ (30 mL)

Alcohol 9% v/v

Sunway Biotech SCIENTIFICALLY TESTED

PURPOSE

Echinacea with Energy Medicine with DNA